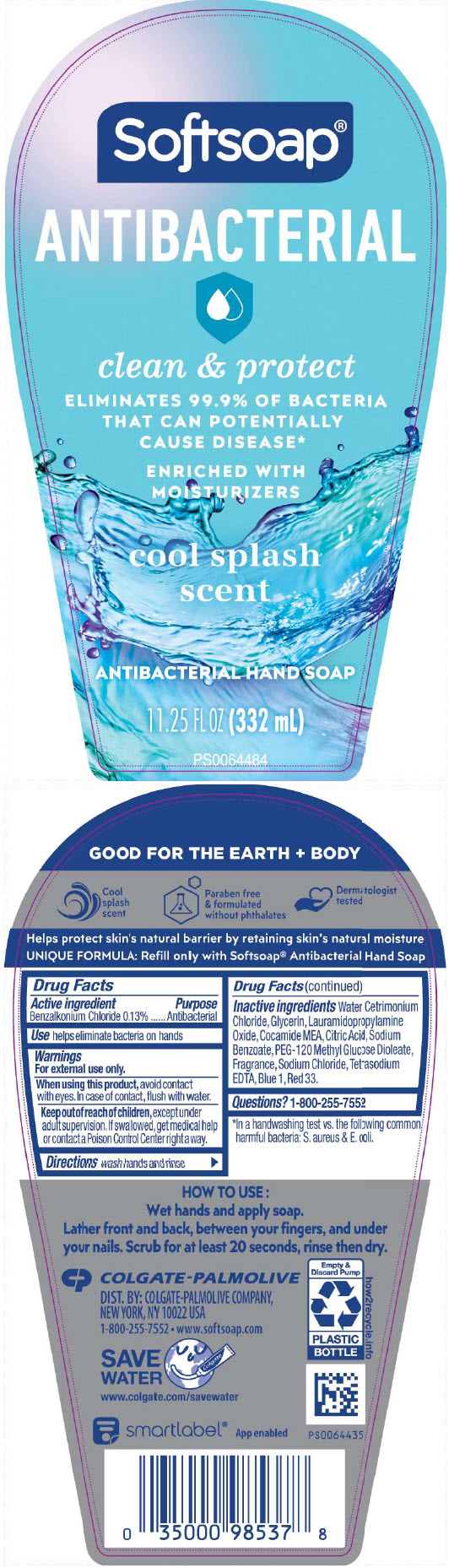 DRUG LABEL: Softsoap Antibacterial Clean and Protect Cool Splash
NDC: 35000-254 | Form: LIQUID
Manufacturer: COLGATE PALMOLIVE COMPANY
Category: otc | Type: HUMAN OTC DRUG LABEL
Date: 20241113

ACTIVE INGREDIENTS: BENZALKONIUM CHLORIDE 1.33 mg/1 mL
INACTIVE INGREDIENTS: WATER; CETRIMONIUM CHLORIDE; GLYCERIN; LAURAMIDOPROPYLAMINE OXIDE; COCO MONOETHANOLAMIDE; ANHYDROUS CITRIC ACID; SODIUM BENZOATE; PEG-120 METHYL GLUCOSE DIOLEATE; SODIUM CHLORIDE; EDETATE SODIUM; FD&C BLUE NO. 1; D&C RED NO. 33

Softsoap Antibacterial Clean & Protect Cool Splash

Drug Facts

Active ingredient

Benzalkonium Chloride 0.13%

Purpose

Antibacterial

Use

helps eliminate bacteria on hands

Warnings

For external use only.

When using this product, avoid contact with eyes.

In case of contact, flush with water.

Keep out of reach of children, except under adult supervision. If swallowed, get medical help or contact a Poison Control Center right away.

Directions

wash hands and rinse

Inactive ingredients

Water, Cetrimonium Chloride, Glycerin, Lauramidopropylamine Oxide, Cocamide MEA, Citric Acid, Sodium Benzoate, PEG-120 Methyl Glucose Dioleate, Fragrance, Sodium Chloride, Tetrasodium EDTA, Blue 1, Red 33.

Questions?

1-800-255-7552

DIST. BY: COLGATE-PALMOLIVE COMPANY,
NEW YORK, NY 10022 USA

PRINCIPAL DISPLAY PANEL - 332 mL Bottle Label

Softsoap®

ANTIBACTERIAL

clean & protect

ELIMINATES 99.9% OF BACTERIA
THAT CAN POTENTIALLY
CAUSE DISEASE*

ENRICHED WITH
MOISTURIZERS

cool splash
scent

ANTIBACTERIAL HAND SOAP

11.25 FL OZ (332 mL)

PS0064484